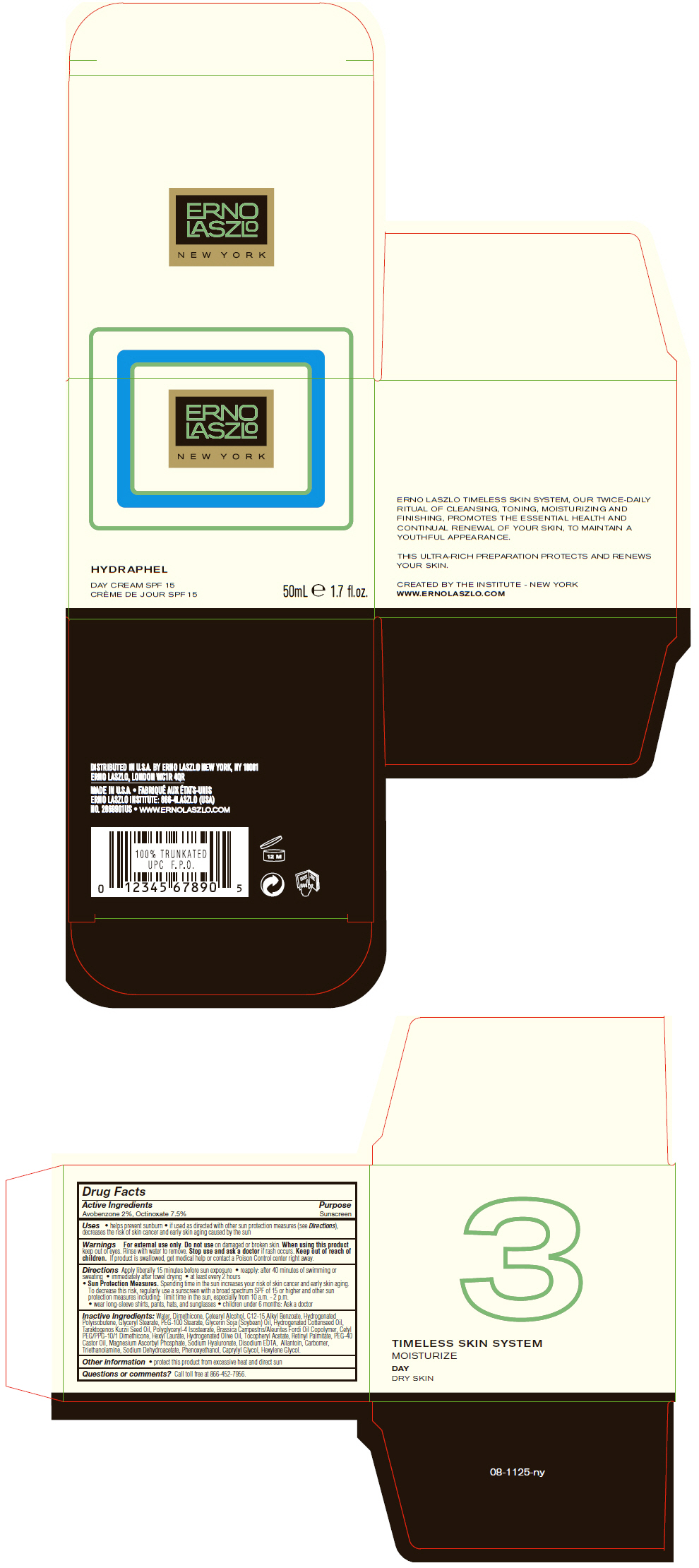 DRUG LABEL: Hydraphel Day  SPF15
NDC: 57913-2869 | Form: CREAM
Manufacturer: Erno Laszlo, Inc.
Category: otc | Type: HUMAN OTC DRUG LABEL
Date: 20130408

ACTIVE INGREDIENTS: Avobenzone 20 mg/1 mL; Octinoxate 75 mg/1 mL
INACTIVE INGREDIENTS: Water; Dimethicone; Cetostearyl Alcohol; Alkyl (C12-15) Benzoate; Glyceryl Monostearate; Soybean Oil; Hydrogenated Cottonseed Oil; Hydnocarpus Kurzii Seed Oil; Polyglyceryl-4 Isostearate; Hexyl Laurate; .Alpha.-Tocopherol Acetate; Vitamin A Palmitate; PEG-40 Castor Oil; Magnesium Ascorbyl Phosphate; Hyaluronate Sodium; Edetate Disodium; Allantoin; Trolamine; Sodium Dehydroacetate; Phenoxyethanol; Caprylyl Glycol; Hexylene Glycol

Hydraphel Day SPF15

Drug Facts

Active Ingredients

Avobenzone 2%, Octinoxate 7.5%

Purpose

Sunscreen

Uses

- helps prevent sunburn
- if used as directed with other sun protection measures (see Directions), decreases the risk of skin cancer and early skin aging caused by the sun

Warnings

For external use only.

Do not use on damaged or broken skin.

When using this product keep out of eyes. Rinse with water to remove.

Stop use and ask a doctor if rash occurs.

Keep out of reach of children. If product is swallowed, get medical help or contact a Poison Control center right away.

Directions

Apply liberally 15 minutes before sun exposure

- reapply: after 40 minutes of swimming or sweating
- immediately after towel drying
- at least every 2 hours
- Sun Protection Measures. Spending time in the sun increases your risk of skin cancer and early skin aging. To decrease this risk, regularly use a sunscreen with a broad spectrum SPF of 15 or higher and other sun protection measures including: limit time in the sun, especially from 10 a.m. - 2 p.m.
  - wear long-sleeve shirts, pants, hats, and sunglasses
  - children under 6 months: Ask a doctor

Inactive Ingredients

Water, Dimethicone, Cetearyl Alcohol, C12-15 Alkyl Benzoate, Hydrogenated Polyisobutene, Glyceryl Stearate, PEG-100 Stearate, Glycerin Soja (Soybean) Oil, Hydrogenated Cottenseed Oil, Taraktogenos Kurzii Seed Oil, Polyglyceryl-4 Isostearate, Brassica Campestris/Aleurites Fordi Oil Copolymer, Cetyl PEG/PPG-10/1 Dimethicone, Hexyl Laurate, Hydrogenated Olive Oil, Tocopheryl Acetate, Retinyl Palmitate, PEG-40 Castor Oil, Magnesium Ascorbyl Phosphate, Sodium Hyaluronate, Disodium EDTA, Allantoin, Carbomer, Triethanolamine, Sodium Dehydroacetate, Phenoxyethanol, Caprylyl Glycol, Hexylene Glycol.

Other information

- protect this product from excessive heat and direct sun

Questions or comments?

Call toll free at 866-452-7956.

DISTRIBUTED IN U.S.A. BY ERNO LASZLO NEW YORK, NY 10001

PRINCIPAL DISPLAY PANEL - 50 mL Jar Carton

ERNO
LASZLO

NEW YORK

HYDRAPHEL

DAY CREAM SPF 15

50mL e 1.7 fl.oz.